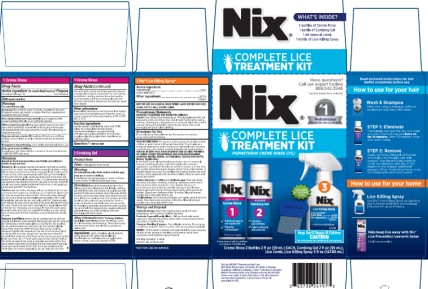 DRUG LABEL: Nix Complete Lice Treatment
NDC: 63736-035 | Form: KIT | Route: TOPICAL
Manufacturer: Insight Pharmaceuticals LLC
Category: otc | Type: HUMAN OTC DRUG LABEL
Date: 20251023

ACTIVE INGREDIENTS: PERMETHRIN 280 mg/100 mL; PERMETHRIN 25 mg/1 mL
INACTIVE INGREDIENTS: METHYLPARABEN; PROPYLPARABEN; CANADA BALSAM; CETYL ALCOHOL; ANHYDROUS CITRIC ACID; FD&C YELLOW NO. 6; HYDROXYETHYL CELLULOSE, UNSPECIFIED; CETETH-10; PROPYLENE GLYCOL; STEARALKONIUM CHLORIDE; WATER; ISOPROPYL ALCOHOL; POLYQUATERNIUM-10 (125 MPA.S AT 2%); WATER; PROPYLENE GLYCOL; GLYCERIN; DIAZOLIDINYL UREA; HYDROXYETHYL CELLULOSE, UNSPECIFIED; TRISODIUM CITRATE DIHYDRATE; CITRIC ACID MONOHYDRATE; METHYLPARABEN; PROPYLPARABEN; EDETATE DISODIUM ANHYDROUS; WATER 75 mg/1 mL

Nix Complete Lice Treatment Kit

[1 Eliminate] Creme Rinse

Drug Facts

Active ingredient (in each fluid ounce)

Permethrin 280 mg (1%)

Purpose

Lice treatment

Uses

treats head lice

Warnings

For external use only

Do not use

- on children under 2 months of age
- near the eyes
- inside the nose, ear, mouth, or vagina
- on lice in eyebrows or eyelashes.
  See your doctor.

Ask a doctor before use if you are

- allergic to ragweed. May cause breathing difficulty or an asthmatic episode.

When using this product

- keep eyes tightly closed and protect eyes with a washcloth or towel
- if product gets into the eyes, immediately flush with large amounts of water
- scalp itching or redness may occur

Stop use and ask a doctor if

- breathing difficulty occurs
- eye irritation occurs
- skin or scalp irritation continues or infection occurs

If pregnant or breast-feeding,

ask a health professional before use.

Keep out of reach of children.

If swallowed, get medical help or contact a Poison Control Center (1-800-222-1222) right away.

Directions

Important: Read warnings before use

- Adults and children 2 months old and older

Inspect

- all household members should be checked by another person for lice and/or nits (eggs)
- use a magnifying glass in bright light to help you see the lice and/or nits (eggs)
- use a tool, such as a comb or two unsharpened pencils to lift and part the hair
- look for tiny nits near scalp, beginning at back of neck and behind ears
- small sections of hair (1-2 inches wide) should be examined at a time
- unlike dandruff, nits stick to the hair. Dandruff should move when lightly touched,
- if either lice or nits (or eggs) are found, treat with Nix® Creme Rinse

Treat

- wash hair with a shampoo without conditioner. Do not use a shampoo that contains a conditioner or a conditioner alone since this may decrease the activity of Nix®. Rinse with water.
- towel dry hair so it is damp but not wet
- shake the bottle of Nix® well
- completely saturate the hair and scalp with Nix®. Begin to apply Nix® behind the ears and at the back of the neck.
- keep Nix® out of the eyes. Protect the eyes with a washcloth or towel.
- leave Nix® on the hair for 10 minutes, but no longer
- rinse with warm water
- towel dry hair and comb out tangles
- if live lice are seen seven days or more after the first treatment, a second treatment should be given

Remove Lice/Nits

- remove nits by combing the hair with the special small tooth comb provided. Remaining nits may be removed by hand (using a throw-away glove), or cutting the nits out.
- use the nit comb provided and make sure the hair remains slightly damp while removing nits
- if the hair dries during combing, dampen it slightly with water
- part the hair into 4 sections. Work on one section at a time. Longer hair may take more time (1-2 hours).
- start at the top of the head on the section you have picked
- with one hand, lift a 1-2 inch wide strand of hair. Get the teeth of the comb as close to the scalp as possible and comb with a firm, even motion away from the scalp to the end of the hair.
- use clips to pin back each strand of hair after you have combed out the nits
- clean the comb completely as you go. Wipe the nits from the comb with a tissue and throw away the tissue in a sealed plastic bag to prevent the lice from coming back.
- after combing, recheck the entire head for nits and repeat combing if necessary
- check the affected head daily to remove any nits that you might have missed

Other information

- read all the directions in the Consumer Information Insert and warnings before use. Keep the carton. It contains important information.
- store at 20° to 25°C (68° to 77°F)

Inactive ingredients

balsam canada, cetyl alcohol, citric acid, FD&C yellow no. 6, fragrance, hydrolyzed animal protein, hydroxyethylcellulose, polyoxyethylene 10 cetyl ether, propylene glycol, stearalkonium chloride, water, isopropyl alcohol, methylparaben, propylparaben

Questions?

1-888-542-3546

[2 Remove] Combing Gel & Comb

Product Facts

Uses

To detangle and comb the hair

Warnings

For external use only. Avoid contact with the eyes.

Keep out of reach of children.

If swallowed, get medical help or contact a Poison Control Center (1-800-222-1222) right away.

Directions

- use after shampooing with lice killing creme rinse
- towel dry hair
- apply combining gel until all the hair and scalp is thoroughly wet with product
- make sure product covers the area behind the ears and at the nape of the neck where there are more likely to be nits
- part hair into sections and clip back
- use the enclosed special-toothed comb to comb out dead lice and nits
- comb out one section at a time
- it is extremely important to comb out dead lice and nits
- if hair begins to dry, reapply additional product
- when you finish combing, rinse hair thoroughly with warm water.

Other Information

- Nix Combing Gel does not kill lice and nits
- Pesticide free
- Keep carton for full information and warnings. Read all warnings and directions before use.
- Visit our website at nixlice.com

Ingredients

water, propylene glycol, glycerin, polyquaternium-10, diazolidinyl urea, hydroxyethylcellulose, sodium citrate dihydrate, citric acid, methylparaben, propylparaben, disodium EDTA

[3 Control] Nix ® Lice Control Spray

Active ingredient:

PERMETHRIN 0.25%

(CAS # 52645-53-1)

Other ingredients:

99.75%

100.00%

NOT FOR USE ON HUMANS. READ ENTIRE LABEL BEFORE EACH USE. SHAKE BOTTLE WELL BEFORE USING.

Precautionary Statements

Hazards to Humans and Domestic Animals

Caution User Safety Recommendations: Wear long-sleeved shirt and long pants, socks and shoes. User should wash hands before eating, drinking, chewing gum, using tobacco, or using the toilet. User should remove clothing immediately if pesticide gets inside. Then wash thoroughly and put on clean clothing.

Directions For Use

It is a violation of Federal law to use this product in a manner inconsistent with its labeling.

User Restrictions: For use as a surface spray, do not allow adults, children or pets to enter until sprays have dried. Do not apply as a broadcast treatment to indoor surfaces at residential sites, including nurseries, day care centers, schools, hospitals and nursing homes.

FOR USE IN NON-FOOD AREAS INDOORS AND OUTSIDE PREMISES OF HOMES, HOBBY GREENHOUSES AND STORAGE BUILDINGS, CAMPERS, MOBILE HOMES, AUTOMOBILES, TRUCKS AND BOATS.

Indoor Application

In the home, cover all food handling surfaces, cover or remove all food and cooking utensils or wash thoroughly after treatment. Application is prohibited directly into sewers or drains, or to any area like a gutter where drainage to sewers, storm drains, water bodies, or aquatic habitat can occur. Do not allow the product to enter any drain during or after application. Do not enter or allow others to enter until sprays have dried.

Surface Spraying: To kill lice and nits/ louse eggs: Treat only those garments and parts of bedding, including mattresses and furniture that cannot be either laundered or dry cleaned. Spray in an inconspicuous area to test for possible staining or discoloration. Inspect again after drying, then proceed to spray entire area to be treated. Spray from a distance of 8 to 10 inches. Allow all treated articles to dry thoroughly before use.

To kill bedbugs: Spray mattresses lightly, particularly around tufts and seams. Take beds apart and spray in all joints. Allow all sprayed articles to dry thoroughly before use.

Storage and Disposal

Pesticide Storage: Keep from freezing. Store upright at room temperature, out of reach of children and pets.

Pesticide Disposal: If partly filled – Call your local solid waste agency for disposal instructions. Never place unused product down any indoor or outdoor drain.

Container Handling: If empty – Nonrefillable container. Do not reuse or refill this container. Place in trash or offer for recycling if available.

NOTICE: To the extent consistent with applicable law, buyer assumes all risks of use, storage or handling of this product not in strict accordance with directions given herewith.

EPA REG. NO. 64321-1-75406

EPA EST. NO. 91705-NJ-001

PRINCIPAL DISPLAY PANEL

Nix® Complete Lice Treatment Kit
Permethrin Creme Rinse (1%)
Creme Rinse 2 Bottles 2 fl oz (59 mL) EACH, Combing Gel 2 fl oz (59 mL), Lice Comb, Lice Control Spray 5 fl oz (147.86 mL)